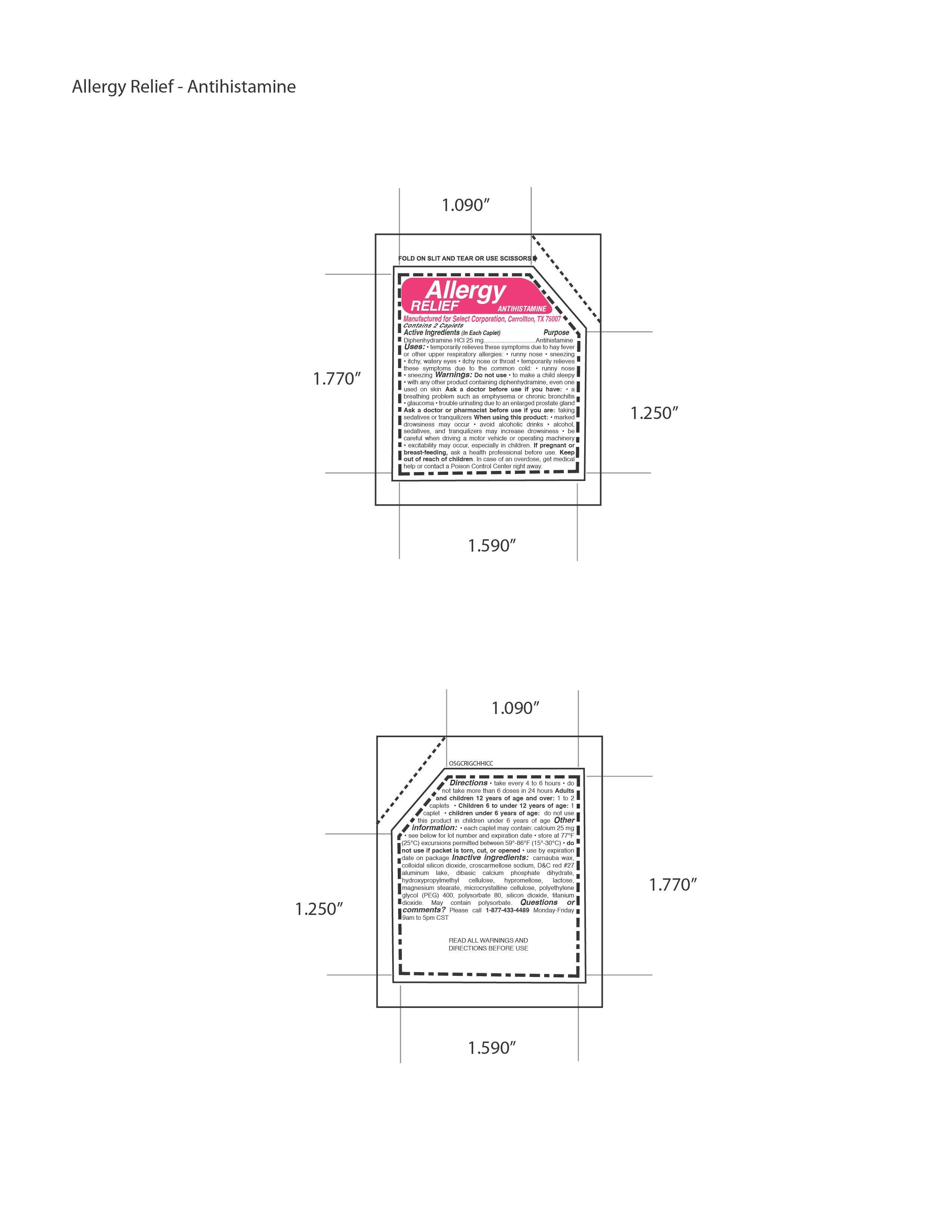 DRUG LABEL: Allergy Antihistamine
                
NDC: 52904-460 | Form: TABLET
Manufacturer: Select Corporation
Category: otc | Type: HUMAN OTC DRUG LABEL
Date: 20121015

ACTIVE INGREDIENTS: DIPHENHYDRAMINE HYDROCHLORIDE 25 mg/1 1
INACTIVE INGREDIENTS: TITANIUM DIOXIDE; POLYSORBATE 80; CARNAUBA WAX; POLYETHYLENE GLYCOL 300; CELLULOSE, MICROCRYSTALLINE; MAGNESIUM STEARATE; CROSCARMELLOSE SODIUM; SILICON DIOXIDE; LACTOSE; D&C RED NO. 27

Drug Facts

Active Ingredients

Diphenhydramine HCl 25 mg

PURPOSE

Antihistamine

DOSAGE AND ADMINISTRATION

Directions • take every 4 to 6 hours • do
not take more than 6 doses in 24 hours Adults
and children 12 years of age and over: 1 to 2
caplets • Children 6 to under 12 years of age: 1
caplet • children under 6 years of age: do not use
this product in children under 6 years of age

INDICATIONS AND USAGE

Uses: • temporarily relieves these symptoms due to hay fever
or other upper respiratory allergies: • runny nose • sneezing
• itchy, watery eyes • itchy nose or throat • temporarily relieves
these symptoms due to the common cold: • runny nose
• sneezing

WARNINGS

Warnings: Do not use • to make a child sleepy
• with any other product containing diphenhydramine, even one
used on skin Ask a doctor before use if you have: • a
breathing problem such as emphysema or chronic bronchitis
• glaucoma • trouble urinating due to an enlarged prostate gland
Ask a doctor or pharmacist before use if you are: taking
sedatives or tranquilizers When using this product: • marked
drowsiness may occur • avoid alcoholic drinks • alcohol,
sedatives, and tranquilizers may increase drowsiness • be
careful when driving a motor vehicle or operating machinery
• excitability may occur, especially in children.

PREGNANCY OR BREAST FEEDING

If pregnant or
breast-feeding, ask a health professional before use.

KEEP OUT OF REACH OF CHILDREN.

Inactive ingredients: carnauba wax,
colloidal silicon dioxide, croscarmellose sodium, DC red 27
aluminum lake, dibasic calcium phosphate dihydrate,
hydroxypropylmethyl cellulose, hypromellose, lactose,
magnesium stearate, microcrystalline cellulose, polyethylene
glycol (PEG) 400, polysorbate 80, silicon dioxide, titanium
dioxide

PACKAGE LABEL

MM1